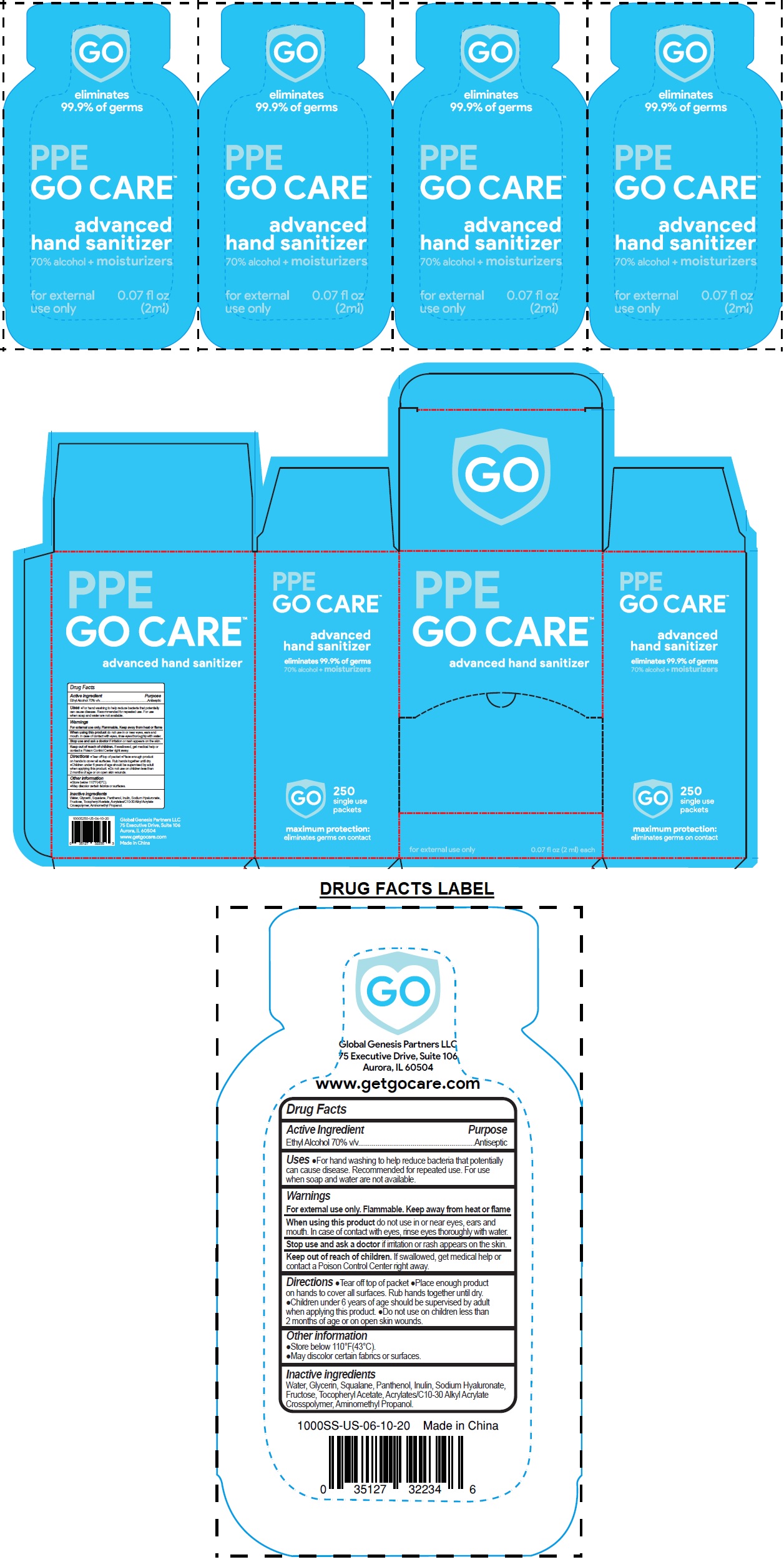 DRUG LABEL: GO CARE advanced hand sanitizer
NDC: 79110-141 | Form: GEL
Manufacturer: Global Genesis Partners Llc
Category: otc | Type: HUMAN OTC DRUG LABEL
Date: 20200713

ACTIVE INGREDIENTS: ALCOHOL 0.7 mL/1 mL
INACTIVE INGREDIENTS: WATER; GLYCERIN; SQUALANE; PANTHENOL; INULIN; HYALURONATE SODIUM; FRUCTOSE; .ALPHA.-TOCOPHEROL ACETATE; CARBOMER INTERPOLYMER TYPE A (ALLYL SUCROSE CROSSLINKED); AMINOMETHYLPROPANOL

GO CARE™ advanced hand sanitizer

Active Ingredient

Ethyl Alcohol 70% v/v

Purpose

Antiseptic

INDICATIONS AND USAGE

Uses •For hand washing to help reduce bacteria that potentially can cause disease. Recommended for repeated use. For use when soap and water are not available.

Warnings

For external use only. Flammable. Keep away from heat or flame

When using this product do not use in or near eyes, ears and mouth. In case of contact with eyes, rinse eyes thoroughly with water.

Stop use and ask a doctor if irritation or rash appears on the skin.

Keep out of reach of children. If swallowed, get medical help or contact a Poison Control Center right away.

DOSAGE AND ADMINISTRATION

Directions •Tear off top of packet •Place enough product on hands to cover all surfaces. Rub hands together until dry. •Children under 6 years of age should be supervised by adult when applying this product. •Do not use on children less than 2 months of age or on open skin wounds.

Other information

- Store below 110°F (43°C).
- May discolor certain fabrics or surfaces.

Inactive ingredients

Water, Glycerin, Squalane, Panthenol, Inulin, Sodium Hyaluronate, Fructose, Tocopheryl Acetate, Acrylates/C10-30 Alkyl Acrylate Crosspolymer, Aminomethyl Propanol.

GO

eliminates 99.9% of germs

maximum protection:

eliminates germs on contact

70% alcohol + moisturizers

For external use only

Global Genesis partners LLC

75 Executive Drive, Suite 106

Aurora, IL 60504

www.getgocare.com

Made in China